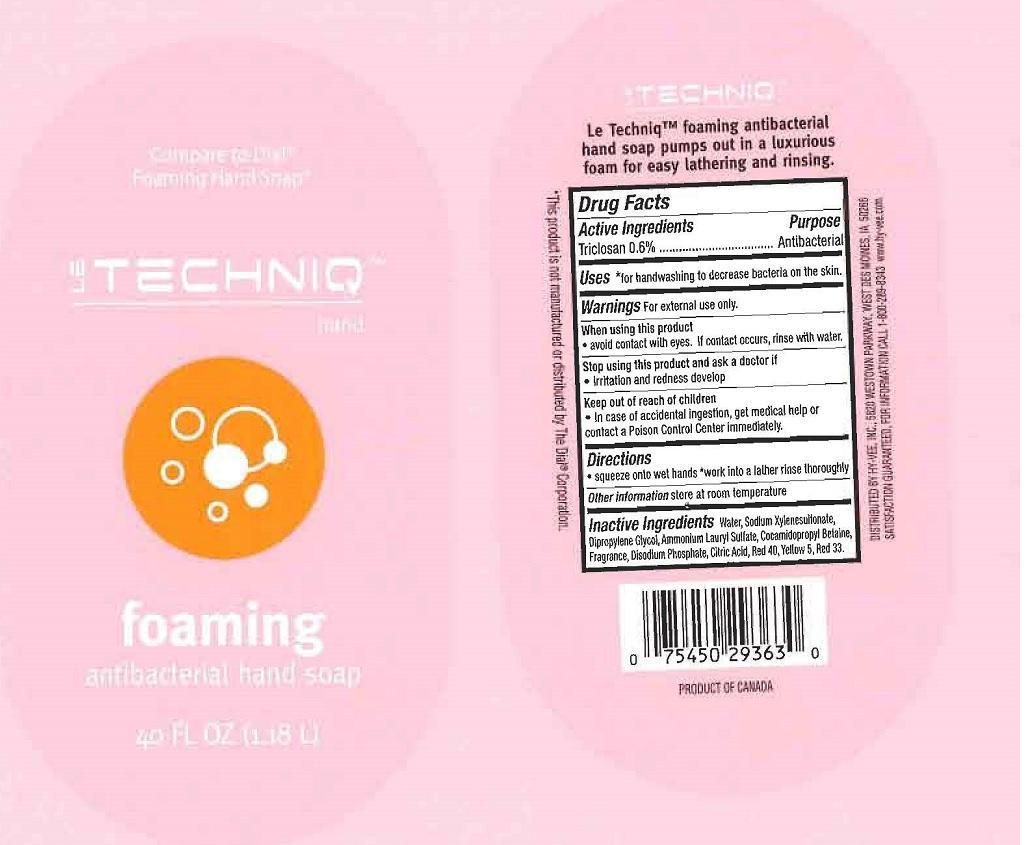 DRUG LABEL: LE TECHNIQ
NDC: 42507-168 | Form: LIQUID
Manufacturer: HYVEE INC
Category: otc | Type: HUMAN OTC DRUG LABEL
Date: 20140226

ACTIVE INGREDIENTS: TRICLOSAN 6 mg/1 mL
INACTIVE INGREDIENTS: WATER; SODIUM XYLENESULFONATE; DIPROPYLENE GLYCOL; AMMONIUM LAURYL SULFATE; COCAMIDOPROPYL BETAINE; SODIUM PHOSPHATE, DIBASIC ANHYDROUS; CITRIC ACID MONOHYDRATE; FD&C RED NO. 40; FD&C YELLOW NO. 5; D&C RED NO. 33

DRUG FACTS

ACTIVE INGREDIENTS

TRICLOSAN 0.6%

PURPOSE

ANTIBACTERIAL

USES

FOR HANDWASHING TO DECREASE BACTERIA ON THE SKIN

WARNINGS

FOR EXTERNAL USE ONLY

WHEN USING THIS PRODUCT

AVOID CONTACT WITH EYES. IF CONTACT OCCURS, RINSE WITH WATER

STOP USING THIS PRODUCT AND ASK A DOCTOR IF

IRRITATION AND REDNESS DEVELOP

KEEP OUT OF REACH OF CHILDREN

IN CASE OF ACCIDENTAL INGESTION, GET MEDICAL HELP OR CONTACT A POISON CONTROL CENTER IMMEDIATELY

DIRECTIONS

SQUEEZE ONTO WET HANDS. WORK INTO A LATHER RINSE THOROUGHLY

OTHER INFORMATION

STORE AT ROOM TEMPERATURE

INACTIVE INGREDIENTS

WATER, SODIUM XYLENESULFONATE, DIPROPYLENE GLYCOL, AMMONIUM LAURYL SULFATE, COCAMIDOPROPYL BETAINE, FRAGRANCE, DISODIUM PHOSPHATE, CITRIC ACID, RED 40, YELLOW 5, RED 33